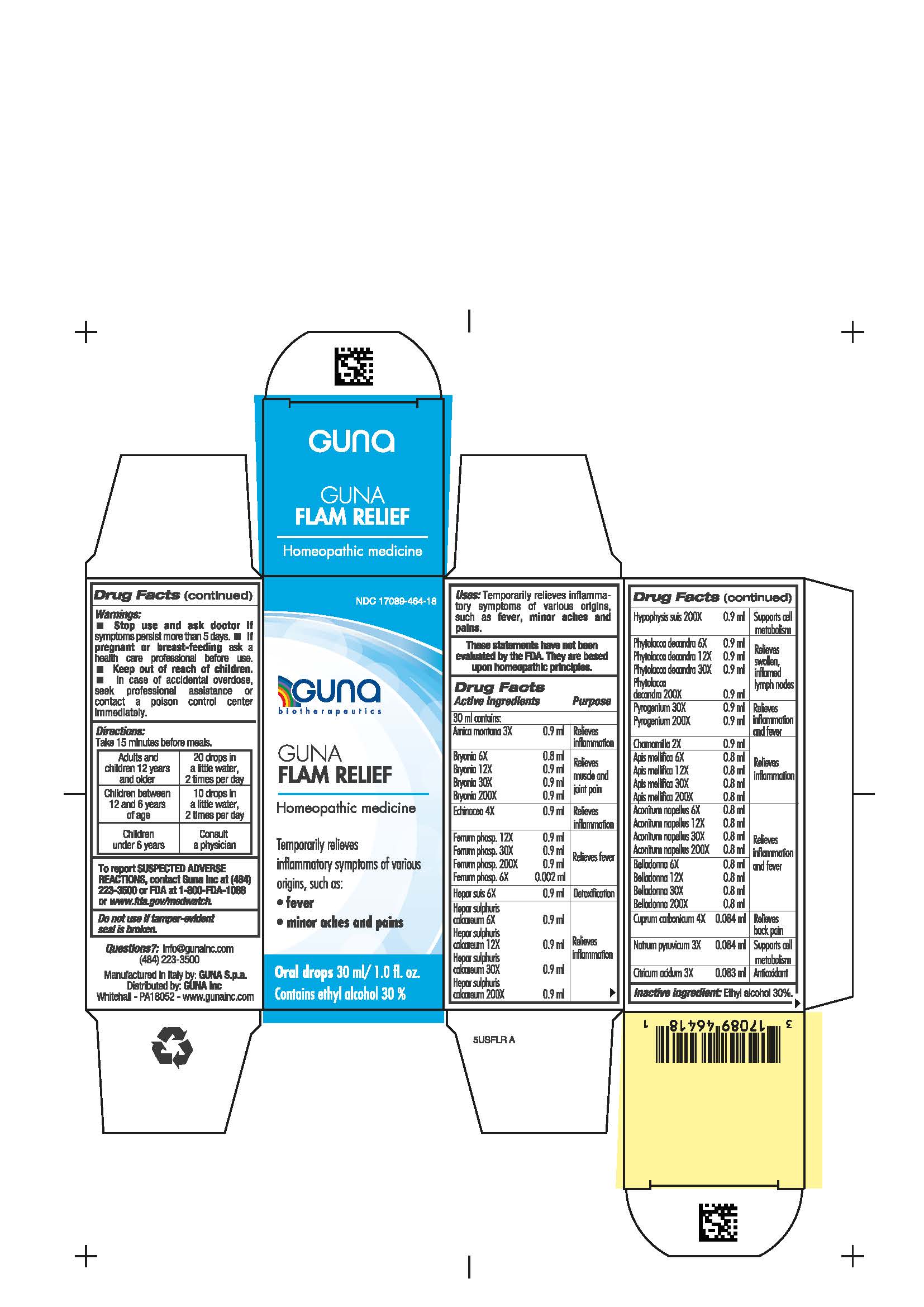 DRUG LABEL: GUNA FLAM RELIEF
NDC: 17089-464 | Form: SOLUTION/ DROPS
Manufacturer: Guna spa
Category: homeopathic | Type: HUMAN OTC DRUG LABEL
Date: 20200915

ACTIVE INGREDIENTS: ARNICA MONTANA 3 [hp_X]/30 mL; ECHINACEA ANGUSTIFOLIA WHOLE 4 [hp_X]/30 mL; RANCID BEEF 30 [hp_X]/30 mL; BASIC CUPRIC CARBONATE 4 [hp_X]/30 mL; MATRICARIA CHAMOMILLA WHOLE 2 [hp_X]/30 mL; ACONITUM NAPELLUS WHOLE 6 [hp_X]/30 mL; APIS MELLIFERA 6 [hp_X]/30 mL; ATROPA BELLADONNA 6 [hp_X]/30 mL; BRYONIA ALBA ROOT 6 [hp_X]/30 mL; CITRIC ACID MONOHYDRATE 3 [hp_X]/30 mL; FERRIC PHOSPHATE 12 [hp_X]/30 mL; CALCIUM SULFIDE 6 [hp_X]/30 mL; SODIUM PYRUVATE 3 [hp_X]/30 mL; PHYTOLACCA AMERICANA ROOT 6 [hp_X]/30 mL; PORK LIVER 6 [hp_X]/30 mL; SUS SCROFA PITUITARY GLAND 200 [hp_X]/30 mL
INACTIVE INGREDIENTS: ALCOHOL

GUNA FLAM RELIEF

Inactive Ingredient: Ethyl alcohol 30%.

PURPOSE

Temporarily relieves inflammatory symptoms of various origins such as:

- fever
- minor aches and pains

QUESTIONS

info@gunainc.com

(484) 223-3500

WARNINGS

Keep this and all medicines out of reach of children

DIRECTIONS

Take 15 minutes before meals

WARNINGS

- Stop use and ask doctor if symptoms persist more than 5 days.
- If pregnant or breast-feeding ask a health care professional before use.
- Keep out of reach of children. In case of overdose, seek professional assistance or contact a Poison Control Center immediately.
- Contains ethyl alcohol 30%

ACTIVE INGREDIENTS/PURPOSE

Arnica montana 3X Relieves inflammation

Bryonia 6X, 12X, 30X, 200X Relieves muscle and joint pain

Echinacea 4X Relieves inflammation

Ferrum phosphoricum 6X, 12X, 30X, 200X Relieves fever

Hepar suis 6X Detoxification

Hepar sulphuris calc. 6X, 12X, 30X, 200X Relieves inflammation

Hypophysis suis 200X Supports cell metabolism

Phytolacca decandra 6X, 12X, 30X, 200X Relieves swollen, inflamed lymph nodes

Pyrogenium 30X, 200X Relieves inflammation and fever

Chamomilla 2X Relieves inflammation

Apis mellifica 6X, 12X, 30X, 200X Relieves inflammation

Aconitum napellus 6X, 12X, 30X, 200X Relieves inflammation and fever

Belladonna 6X, 12X, 30X, 200X Relieves inflammation and fever

Cuprum carbonicum 4X Relieves back pain

Natrum pyruvicum 3X Supports cell metabolism

Citricum acidum 3X Antioxidant

DOSAGE AND ADMINISTRATION

Adults and children twelve years and older: 20 drops in a little water, 2 times per day

Children between 12 and 6 years of age: 10 drops in a little water, 2 times per day

Children under 6 years: consult a physician

PREGNANCY

If pregnant or breast-feeding ask a doctor before use